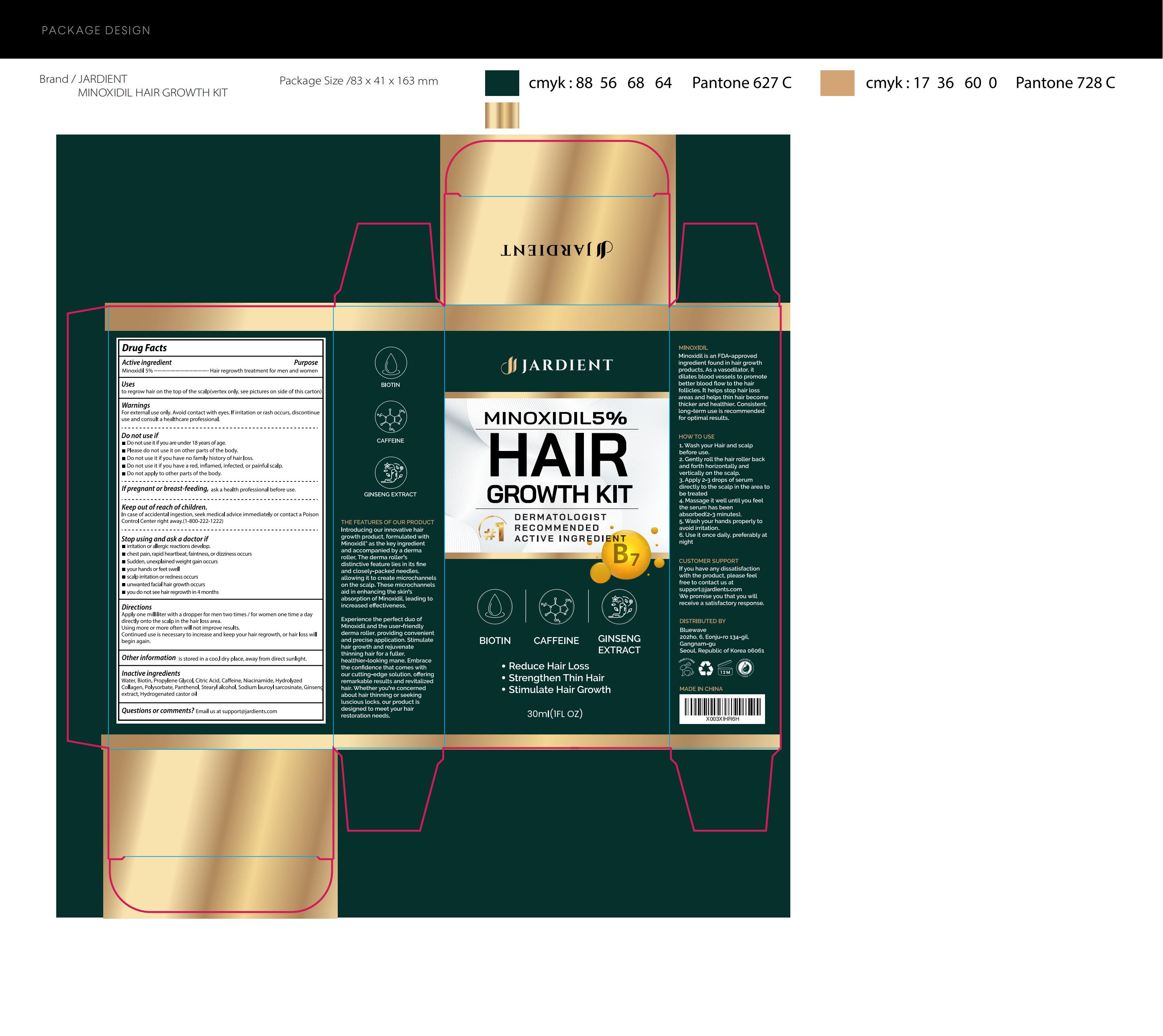 DRUG LABEL: Jardient 5% Minoxidil Hair Growth Serum
NDC: 83596-002 | Form: LIQUID
Manufacturer: Aramode
Category: otc | Type: HUMAN OTC DRUG LABEL
Date: 20231120

ACTIVE INGREDIENTS: MINOXIDIL 5 g/100 mL
INACTIVE INGREDIENTS: CITRIC ACID MONOHYDRATE; NIACINAMIDE; POLYSORBATE 21; SODIUM LAUROYL SARCOSINATE; HYDROGENATED CASTOR OIL; WATER; BIOTIN; PROPYLENE GLYCOL; CAFFEINE; COLLAGEN ALPHA-1(I) CHAIN BOVINE; PANTHENOL; STEARYL ALCOHOL; ASIAN GINSENG

Active Ingredient

Minoxidil 5%

Purpose

Hair regrowth treatment for men and women

Use

to regrow hair on the top of the scalp(vertex only, see pictures on side of this carton)

Warnings

For external use only. Avoid contact with eyes. If irritation or rash occurs, discontinue use and consult a healthcare professional.

Do not use it if you are under 18 years of age.
Please do not use it on other parts of the body.
Do not use it if you have no family history of hair loss.
Do not use it if you have a red, inflamed, infected, or painful scalp.
Do not apply to other parts of the body.

Stop Use

Stop using and ask a doctor if
irritation or allergic reactions develop.
chest pain, rapid heartbeat, faintness, or dizziness occurs
Sudden, unexplained weight gain occurs
your hands or feet swell
scalp irritation or redness occurs
unwanted facial hair growth occurs
you do not see hair regrowth in 4 months

Ask Doctor

Stop using and ask a doctor if
irritation or allergic reactions develop.
chest pain, rapid heartbeat, faintness, or dizziness occurs
Sudden, unexplained weight gain occurs
your hands or feet swell
scalp irritation or redness occurs
unwanted facial hair growth occurs
you do not see hair regrowth in 4 months

Keep Oot Of Reach Of Children

Keep out of reach of children.
In case of accidental ingestion, seek medical advice immediately or contact a Poison Control Center right away.(1-800-222-1222)

Directions

Apply one milliliter with a dropper for men two times / for women one time a day directly onto the scalp in the hair loss area.
Using more or more often will not improve results.
Continued use is necessary to increase and keep your hair regrowth, or hair loss will begin again.

Other information

Store in a cool, dry place, away from direct sunlight.

Inactive ingredients

Water, Biotin, Propylene Glycol, Citric Acid, Caffeine, Niacinamide, Hydrolyzed Collagen, Polysorbate, Panthenol, Stearyl alcohol, Sodium lauroyl sarcosinate, Ginseng extract, Hydrogenated castor oil

Questions

If you are not satisfied with our product, please contact us at Support@jardient.com. We will do our best to resolve any issues you may have.